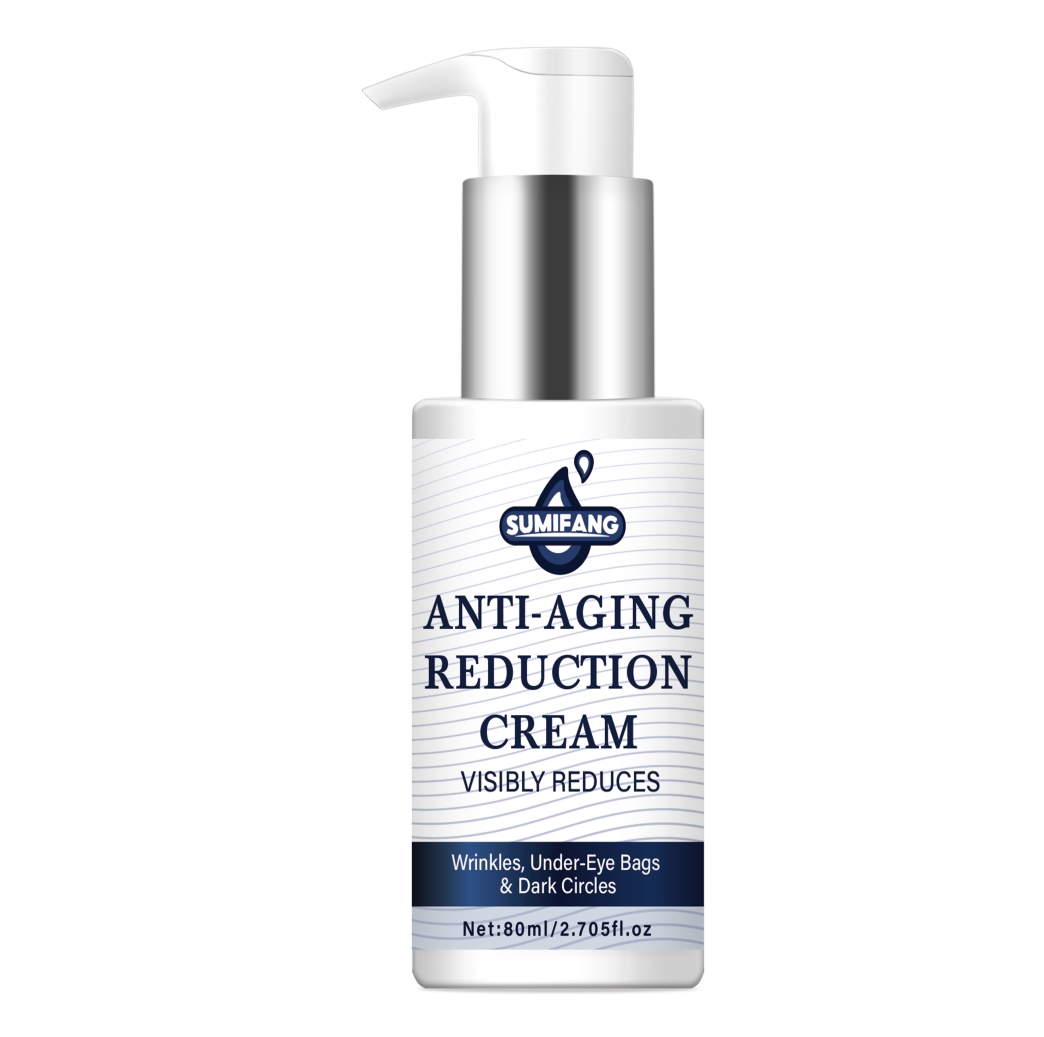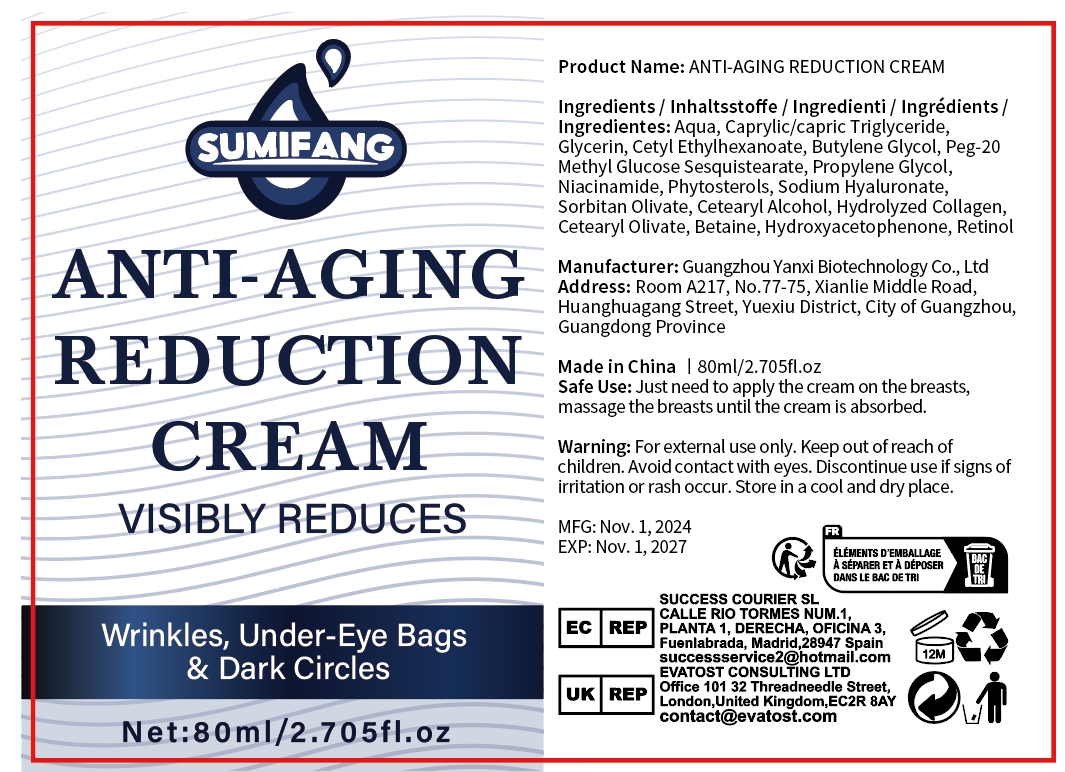 DRUG LABEL: anti-aging reduction cream
NDC: 84025-264 | Form: CREAM
Manufacturer: Guangzhou Yanxi Biotechnology Co., Ltd
Category: otc | Type: HUMAN OTC DRUG LABEL
Date: 20241118

ACTIVE INGREDIENTS: GLYCERIN 3 mg/80 mL; CAPRYLIC/CAPRIC TRIGLYCERIDE 4 mg/80 mL
INACTIVE INGREDIENTS: WATER

DOSAGE AND ADMINISTRATION

Just need to apply the cream on the breasts,massage the breasts until the cream is absorbed.

WARNINGS

Keep out of children

INACTIVE INGREDIENT

Aqua

INDICATIONS AND USAGE

For daily skin care

Keep out of children

PURPOSE

Reduce wrinkles,under-eye bags and dark circles.